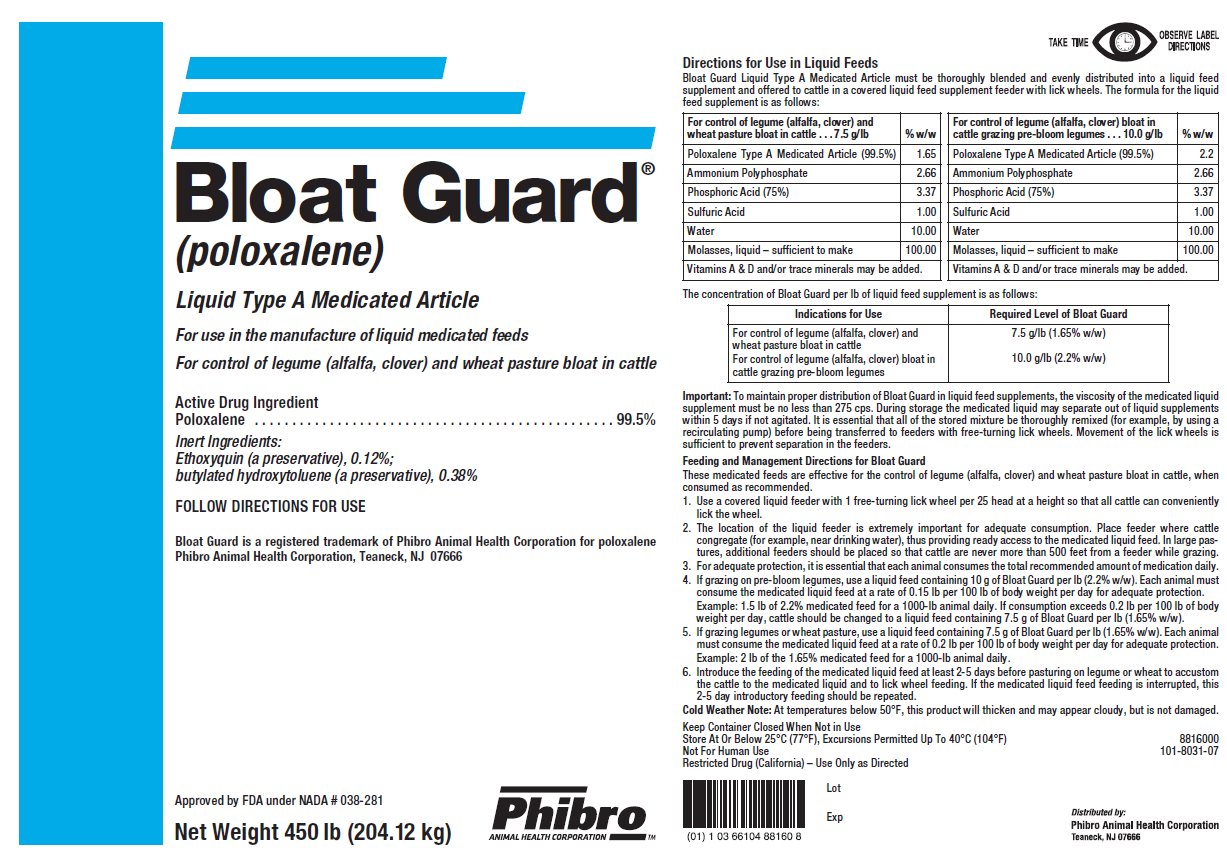 DRUG LABEL: Bloat Guard
NDC: 66104-8816 | Form: LIQUID
Manufacturer: Phibro Animal Health
Category: animal | Type: OTC TYPE A MEDICATED ARTICLE ANIMAL DRUG LABEL
Date: 20190701

ACTIVE INGREDIENTS: POLOXALENE 240.4 g/0.45 kg
INACTIVE INGREDIENTS: BUTYLATED HYDROXYTOLUENE; ETHOXYQUIN

Bloat Guard®
(poloxalene)
Liquid Type A Medicated Article

For use in the manufacture of liquid feed supplements

For control of legume (alfalfa, clover) and wheat pasture bloat in cattle

Active Drug Ingredient

Poloxalene . . . . . . . . . . . . . . . . . . . . . . . . . . . . . . . . . . . . . . . . . . . 99.5%

Inert Ingredients:

Ethoxyquin (a preservative), 0.12%;

butylated hydroxytoluene (a preservative), 0.38%

Follow Directions For Use

Directions for Use in Liquid Feeds

Bloat Guard Liquid Type A Medicated Article must be thoroughly blended and evenly distributed into a liquid feed supplement and offered to cattle in a covered liquid feed supplement feeder with lick wheels. The formula for the liquid feed supplement is as follows:

For control of legume (alfalfa, clover, and wheat pasture bloat in cattle…7.5 g/lb | %w/w | For control of legume (alfalfa, clover) bloat in cattle grazing pre-bloom legumes…10.0 g/lb | % w/w
Poloxalene Type A Medicated Article (99.5%) | 1.65 | Poloxalene Type A Medicated Article (99.5%) | 2.2
Ammonium Polyphosphate | 2.66 | Ammonium Polyphosphate | 2.66
Phosphoric Acid | 3.37 | Phosphoric Acid | 3.37
Sulfuric Acid | 1.00 | Sulfuric Acid | 1.00
Water | 10.00 | Water | 10.00
Molasses, liquid – sufficient to make | 100.00 | Molasses, liquid – sufficient to make | 100.00
Vitamins A&D and/or trace minerals may be added. |  | Vitamins A&D and/or trace minerals may be added.

The concentration of Bloat Guard per lb of liquid feed supplement is as follows:

Indications for Use | Required Level of Bloat Guard
For control of legume (alfalfa, clover) and wheat pasture bloat in cattle; For control of legume (alfalfa, clover) bloat in cattle grazing pre-bloom legumes | 7.5 g/lb (1.65% w/w); 10.0 g/lb (2.2% w/w)

Important:

To maintain proper distribution of Bloat Guard in liquid feed supplements, the viscosity of the medicated liquid supplement must be no less than 275 cps. During storage the medicated liquid may separate out of liquid supplements within 5 days if not agitated. It is essential that all of the stored mixture be thoroughly remixed (for example, by using a recirculating pump) before being transferred to feeders with free-turning lick wheels. Movement of the lick wheels is sufficient to prevent separation in the feeders.

Feeding and Management Directions for Bloat Guard

These medicated supplements are effective for the control of legume (alfalfa, clover) and wheat pasture bloat in cattle, when consumed as recommended.

- Use a covered liquid feeder with 1 free-turning lick wheel per 25 head at a height so that all cattle can conveniently lick the wheel.
- The location of the liquid feeder is extremely important for adequate consumption. Place feeder where cattle congregate (for example, near drinking water), thus providing ready access to the medicated liquid feed supplement. In large pastures, additional feeders should be placed so that cattle are never more than 500 feet from a feeder while grazing.
- For adequate protection, it is essential that each animal consumes the total recommended dosage of medication daily.
- If grazing on pre-bloom legumes, use a liquid feed supplement containing 10 g of Bloat Guard per lb (2.2% w/w). Each animal must consume the medicated liquid feed supplement at a rate of 0.15 lb per 100 lb of body weight per day for adequate protection. Example: 1.5 lb of 2.2% medicated supplement for a 1000-lb animal daily. If consumption exceeds 0.2 lb per 100 lb of body weight per day, cattle should be changed to a liquid feed supplement containing 7.5 g of Bloat Guard per lb (1.65% w/w).
- If grazing legumes or wheat pasture, use a liquid feed supplement containing 7.5 g of Bloat Guard per lb (1.65% w/w). Each animal must consume the medicated liquid feed supplement at a rate of 0.2 lb per 100 lb of body weight per day for adequate protection. Example: 2 lb of the 1.65% medicated supplement for a 1000-lb animal daily.
- Introduce the feeding of the medicated liquid feed supplement at least 2-5 days before pasturing on legume or wheat to accustom the cattle to the medicated liquid supplement and to lick wheel feeding. If the medicated liquid feed supplement feeding is interrupted, this 2-5 day introductory feeding should be repeated.

Cold Weather Note:

At temperatures below 50°F, this product will thicken and may appear cloudy, but is not damaged.

Keep Container Closed When Not in Use

Store At Or Below 25°C (77°F), Excursions Permitted Up To 40°C (104°F)

Not For Human Use

Restricted Drug (California) – Use Only As Directed

Net Weight 450 lb (204.12 kg)

Bloat Guard is a registered trademark of Phibro Animal Health Corporation for poloxalene

Phibro Animal Health, Inc., Teaneck, NJ 07666

Approved by FDA under NADA #038-281

8816000

101-8031-07